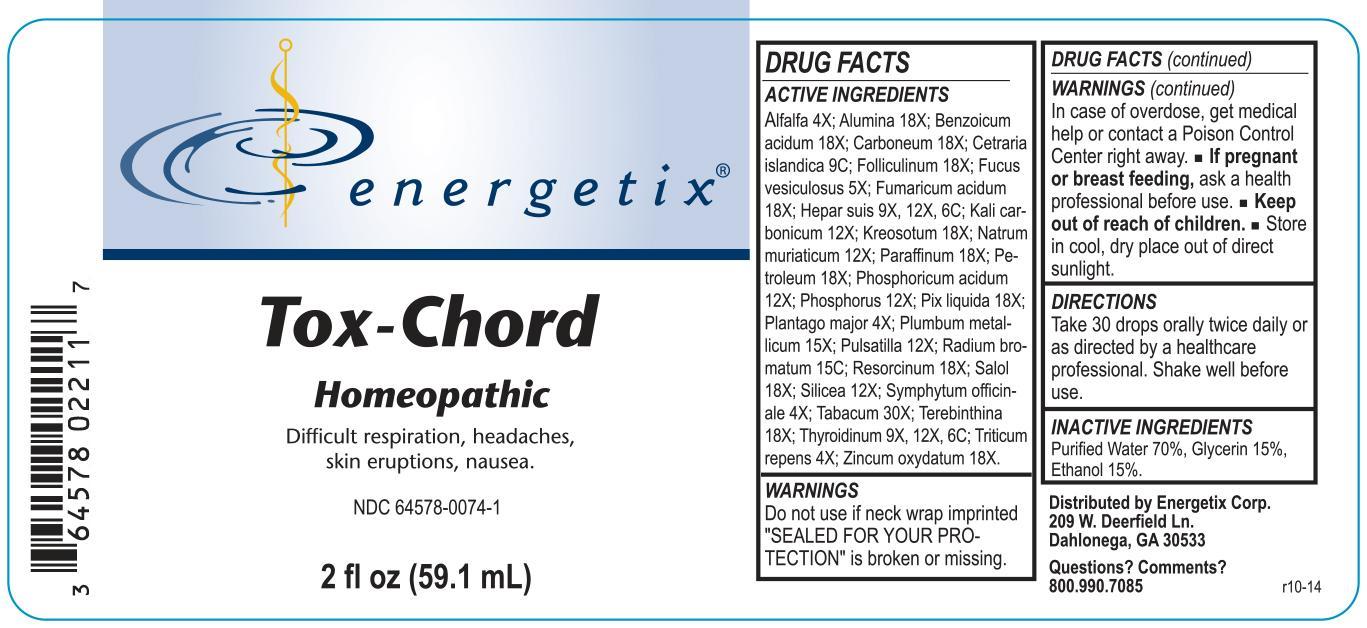 DRUG LABEL: Tox-Chord
NDC: 64578-0074 | Form: LIQUID
Manufacturer: Energetix Corp
Category: homeopathic | Type: HUMAN OTC DRUG LABEL
Date: 20141021

ACTIVE INGREDIENTS: ALFALFA 4 [hp_X]/59.1 mL; ALUMINUM OXIDE 18 [hp_X]/59.1 mL; BENZOIC ACID 18 [hp_X]/59.1 mL; D&C BLACK NO. 2 18 [hp_X]/59.1 mL; CETRARIA ISLANDICA SUBSP. ISLANDICA 9 [hp_C]/59.1 mL; ESTRONE 18 [hp_X]/59.1 mL; FUCUS VESICULOSUS 5 [hp_X]/59.1 mL; FUMARIC ACID 18 [hp_X]/59.1 mL; PORK LIVER 9 [hp_X]/59.1 mL; POTASSIUM CARBONATE 12 [hp_X]/59.1 mL; WOOD CREOSOTE 18 [hp_X]/59.1 mL; SODIUM CHLORIDE 12 [hp_X]/59.1 mL; PARAFFIN 18 [hp_X]/59.1 mL; KEROSENE 18 [hp_X]/59.1 mL; PHOSPHORIC ACID 12 [hp_X]/59.1 mL; PHOSPHORUS 12 [hp_X]/59.1 mL; PINE TAR 18 [hp_X]/59.1 mL; PLANTAGO MAJOR 4 [hp_X]/59.1 mL; LEAD 15 [hp_X]/59.1 mL; PULSATILLA VULGARIS 12 [hp_X]/59.1 mL; RADIUM BROMIDE 15 [hp_C]/59.1 mL; RESORCINOL 18 [hp_X]/59.1 mL; PHENYL SALICYLATE 18 [hp_X]/59.1 mL; SILICON DIOXIDE 12 [hp_X]/59.1 mL; COMFREY ROOT 4 [hp_X]/59.1 mL; TOBACCO LEAF 30 [hp_X]/59.1 mL; TURPENTINE OIL 18 [hp_X]/59.1 mL; THYROID, UNSPECIFIED 9 [hp_X]/59.1 mL; ELYMUS REPENS ROOT 4 [hp_X]/59.1 mL; ZINC OXIDE 18 [hp_X]/59.1 mL
INACTIVE INGREDIENTS: WATER 41.36 mL/59.1 mL; GLYCERIN 8.86 mL/59.1 mL; ALCOHOL 8.86 mL/59.1 mL

Tox-Chord

ACTIVE INGREDIENT

Alfalfa 4X; Alumina 18X; Benzoicum acidum 18X; Carboneum 18X; Cetraria islandica 9C; Folliculinum 18X; Fucus vesiculosus 5X; Fumaricum acidum 18X; Hepar suis 9X, 12X, 6C; Kali carbonicum 12X; Kreosotum 18X; Natrum muriaticum 12X; Paraffinum 18X; Petroleum 18X; Phosphoricum acidum 12X; Phosphorus 12X; Pix liquida 18X; Plantago major 4X; Plumbum metallicum 15X; Pulsatilla 12X; Radium bromatum 15C; Resorcinum 18X; Salol 18X; Silicea 12X; Symphytum officinale 4X; Tabacum 30X; Terebinthina 18X; Thyroidinum 9X, 12X, 6C; Triticum repens 4X; Zincum oxydatum 18X.

Do not use if neck wrap imprinted "SEALED FOR YOUR PROTECTION" is broken or missing.

OVERDOSAGE

In case of overdose, get medical help or contact a Poison Control Center right away.

PREGNANCY OR BREAST FEEDING

If pregnant or breast feeding, ask a health professional before use.

Keep out of reach of children.

STORAGE AND HANDLING

Store in cool, dry place out of direct sunlight.

Questions? Comments?
800.990.7085

PURPOSE

Difficult respiration, headaches, skin eruptions, nausea.

INACTIVE INGREDIENT

Purified Water 70%, Glycerin 15%, Ethanol 15%.

DOSAGE AND ADMINISTRATION

Take 30 drops orally twice daily or as directed by a healthcare professional. Shake well before use.

INDICATIONS AND USAGE

Difficult respiration, headaches, skin eruptions, nausea.